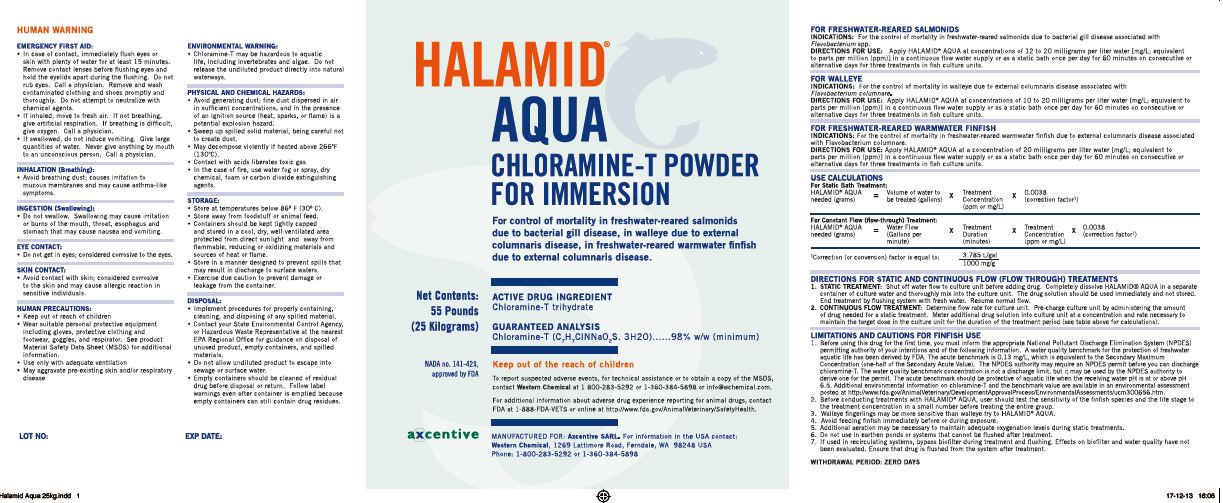 DRUG LABEL: Halamid
NDC: 50378-015 | Form: POWDER
Manufacturer: Western Chemical Inc.
Category: animal | Type: OTC ANIMAL DRUG LABEL
Date: 20141105

ACTIVE INGREDIENTS: CHLORAMINE-T TRIHYDRATE 980 g/1 kg

HALAMID.
AQUACHLORAMINE-T POWDER FOR IMMERSION

FOR FRESHWATER-REARED SAMONOIDS

INDICATIONS: For the control of mortality in freshwater-reared salmonoids due to bacterial gill disease associated with Flavobacterium spp.

DIRECTIONS FOR USE: Apply HALAMID AQUA at concentrations of 12 to 20 milligrams per liter water [mg/L; equivalent to parts per million (ppm)] in a continuous flow water supply or as a static bath once per day for 60 minutes on consecutive or alternative days for three treatments in fish culture units.

FOR WALLEYE

INDICATIONS: For the control of mortality in walleye due to external columnaris disease associated with Flavobacterium columnare

DIRECTIONS FOR USE: Apply HALAMID AQUA at concentrations of 10 to 20 milligrams per liter water [mg/L;equivalent to parts per million (ppm)] in a continuous flow water supply or as a static bath once per day for 60 minutes on consecutive or alternative days for three treatments in fish culture units.

FOR FRESHWATER-REARED WARMWATER FINFISH

INDICATIONS:For the control of mortality in freshwater-reared warmwater finfish due to external columnaris disease associated with Flavobacterium columnare .

DOSAGE AND ADMINISTRATION

DIRECTIONS FOR USE: Apply HALAMID AQUA at a concentration of 20 milligrams per liter water [mg/L; equivalent to parts per million (ppm)] in a continuous flow water supply or as a static bath once per day for 60 minutes on consecutive or alternative days for three treatments in fish culture units.

USE CALCULATIONS

For Static Bath Treatment:
HALAMID.AQUA needed (grams) | = | Volume of water to be treated (gallons) | X | Treatment Concentration (ppm or mg/L) | X | 0.0038 (correction factor) [Correction (or conversion) factor is equal to: 3.785 L/gal/1000 mg/g]
For Constant Flow (flow-through) Treatment:
HALAMID AQUA needed (grams) | = | Water Flow (Gallons per minute) | X | Treatment Duration (minutes) | X | Treatment Concentration (ppm or mg/L) | X | 0.0038 (correction factor)

DIRECTIONS FOR STATIC AND CONTINUOUS FLOW (FLOW THROUGH) TREATMENTS

1. STATIC TREATMENT: Shut off water flow to culture unit before adding drug. Completely dissolve HALAMID AQUA in a separate container of culture water and thoroughly mix into the culture unit. The drug solution should be used immediately and not stored. End treatment by flushing system with fresh water. Resume normal flow.
2. CONTINUOUS FLOW TREATMENT: Determine flow rate for culture unit. Pre-charge culture unit by administering the amount of drug needed for a static treatment. Meter additional drug solution into culture unit at a concentration and rate necessary to maintain the target dose in the culture unit for the duration of the treatment period (see table above for calculations).

LIMITATIONS AND CAUTIONS FOR FINFISH USE

1. Before using this drug for the first time, you must inform the appropriate National Pollutant Discharge Elimination System (NPDES) permitting authority of your intentions and of the following information. A water quality benchmark for the protection of freshwater aquatic life has been derived by FDA. The acute benchmark is 0.13 mg/L, which is equivalent to the Secondary Maximum Concentration (one-half of the Secondary Acute Value). The NPDES authority may require an NPDES permit before you can discharge chloramine-T. The water quality benchmark concentration is not a discharge limit, but it may be used by the NPDES authority to derive one for the permit.The acute benchmark should be protective of aquatic life when the receiving water pH is at or above pH 6.5. Additional environmental information on chloramine-T and the benchmark value are available in an environmental assessment posted at http://www.fda.gov/AnimalVeterinary/DevelopmentApprovalProcess/EnvironmentAssessments/ucm300656.htm.
2. Before conducting treatments with HALAMID AQUA, user should test the sensitivity of the finfish species and the Iife stage to the treatment concentration in a small number before treating the entire group.
3. Walleye fingerlings may be more sensitive than walleye fry to HALAMID AQUA.
4. Avoid feeding finfish immediately before or during exposure
5. Additional aeration may be necessary to maintain adequate oxygenation levels during static treatments
6. Do not use in earthen ponds or systems that cannot be flushed after treatment.
7. If used in recirculating systems, bypass biofilter during treatment and flushing. Effects on biofilter and water quality have not been evaIuated. Ensure that drug is flushed from the system after treatment.

WITHDRAWAL PERIOD: ZERO DAYS

HUMAN WARNING

EMERGENCY FIRST AID:

- In case of contact, immediately flush eyes or skin with plenty of water for at least 15 minutes. Remove contact lenses before flushing eyes and hold the eyelids apart during the flushing. Do not rub eyes. Call a physician. Remove and wash contaminated clothing and shoes promptly and thoroughly. Do not attempt to neutralize with chemical agents.
- If inhaled, move to fresh air. If not breathing, give artificial respiration. If breathing is difficult, give oxygen. Call a physician.
- If swallowed, do not induce vomiting. Give large quantities of water. Never give anything by mouth to an unconscious person. Call a physician.

INHALATION (Breathing):

- Avoid breathing dust; causes irritation to mucous membranes and may cause asthma-like symptoms.

INGESTION (Swallowing):

- Do not swallow. Swallowing may cause irritation or burns of the mouth, throat, esophagus and stomach that may cause nausea and vomiting.

EYE CONTACT:

- Do not get in eyes; considered corrosive to the eyes.

SKIN CONTACT:

- Avoid contact with skin; considered corrosive to skin and may cause allergic reaction in sensitive individuals.

HUMAN PRECAUTIONS:

- Keep out of reach of children
- Wear suitable personal protective equipment including gloves, protective clothing and footwear, googles, and respirator. See product Material Safety Data Sheet (MSDS) for additional information.
- Use only with adequate ventilation
- May aggravate pre-existing skin and/or respiratory disease

ENVIRONMENTAL WARNING:

- Chloramine-T may be hazardous to aquatic life, including invertebrates and algae. Do not release the undiluted product directly into natural waterways.

PHYSICAL AND CHEMICAL HAZARDS:

- Avoid generating dust; fine dust dispersed in air in sufficient concentrations, and in the presence of an ignition source (heat, sparks, or flame) is a potential explosion hazard.
- Sweep up spilled solid material, being careful not to create dust.
- May decompose violently if heated above 266°F (130° C).
- Contact with acids Iiberates toxic gas.
- In the case of fire, use water fog or spray, dry chemical, foam or carbon dioxide extinguishing agents.

STORAGE:

- Store at temperatures below 86° F (30° C).
- Store away from foodstuff or animal feed
- Containers should be kept tightly capped and stored in a cool, dry, well-ventilated area protected from direct sunlight and away from flammable, reducing or oxidizing materials and sources of heat or flame.
- Store in a manner designed to prevent spills that may result in discharge to surface waters.
- Exercise due caution to prevent damage or leakage from the container.

DISPOSAL:

- Implement procedures for properly containing, cleaning, and disposing of any spilled material.
- Contact your State Environmental Control Agency, or Hazardous Waste Representative at the nearest EPA Regional Office for guidance on disposal of unused product, empty containers, and spilled materials.
- Do not allow undiluted product to escape into sewage or surface water.
- Empty containers should be cleaned of residual drug before disposal or return. Follow label warnings even after container is emptied because empty containers can still contain drug residues.

PACKAGE LABEL

HALAMID

AQUA

CHLORAMINE-T POWDER FOR IMMERSION

For control of mortality in freshwater-reared salmonids due to bacterial gill disease, in walleye due to external columnaris disease, in freshwater-reared warmwater finfish due to external columnaris disease

ACTIVE DRUG INGREDIENT
Chloramine-T trihydrate

GUARANTEED ANALYSIS
Chloramine-T (C7H7CINNa02S. 3H20)......98% w/w (minimum}

NET CONTENT:
55 pounds
(25 kilograms)

NADA 141-423,
approved by FDA

Keep out of reach of children

To report suspected adverse events, for technical assistance or to obtain a copy of the MSDS, contact Western Chemical at 1-800-283-5292 or 1-360-384-5898 or info@wchemical.com.

For additional information about adverse drug experience reporting for animal drugs, contact FDA at 1-888-FDA-VETS or online at http://www.fda.gov/AnimalVeterinary/SafetyHealth.

MANUFACTURED FOR : Axcentive SARL. For information in the USA contact: Western Chemical, 1269 Lattimore Road, Ferndale, WA 98248 USA Phone: 1-800-283-5292 or 1-360-384-5898

axcentive